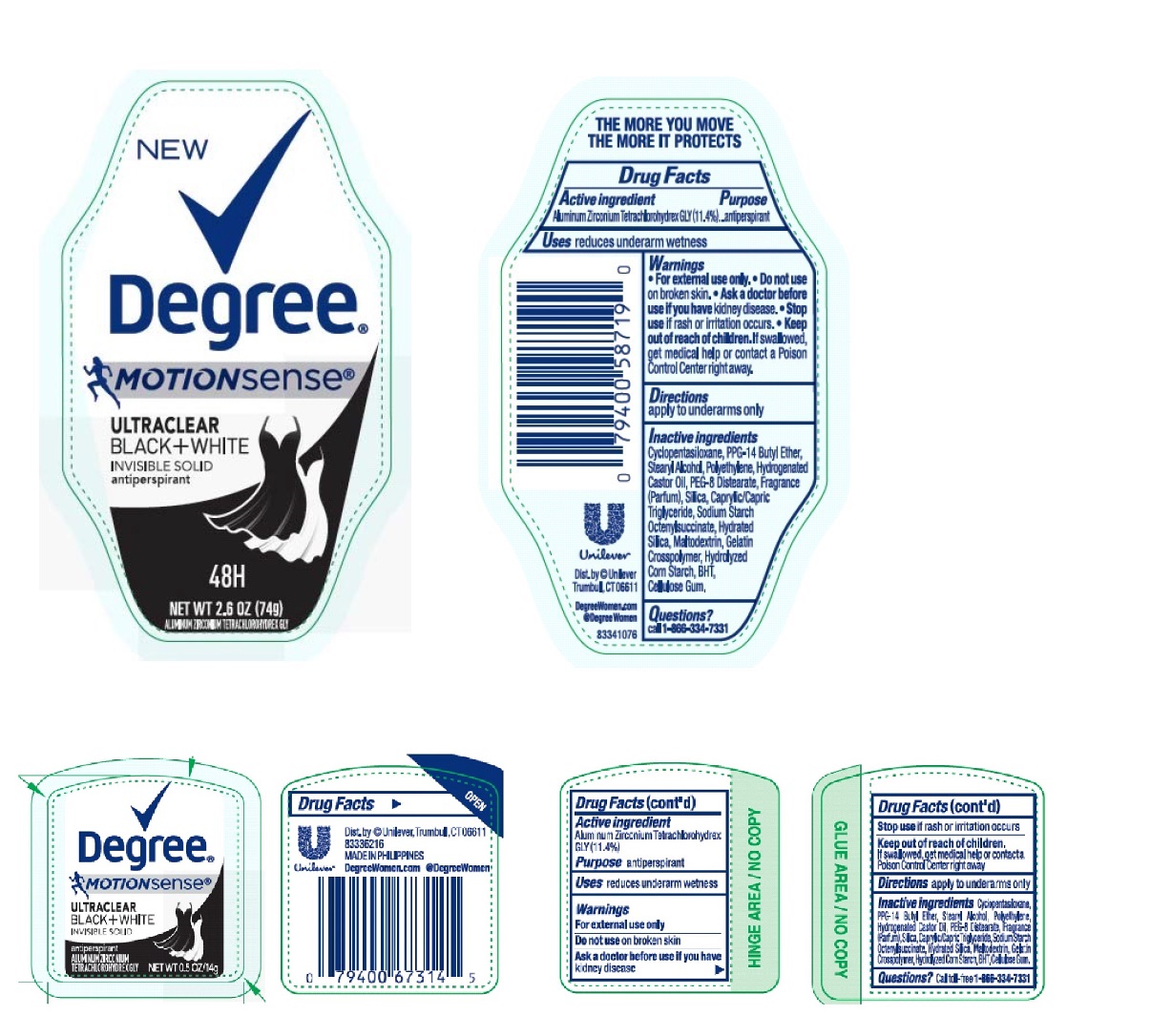 DRUG LABEL: Degree
NDC: 64942-1467 | Form: STICK
Manufacturer: Conopco Inc. d/b/a/ Unilever
Category: otc | Type: HUMAN OTC DRUG LABEL
Date: 20241024

ACTIVE INGREDIENTS: ALUMINUM ZIRCONIUM TETRACHLOROHYDREX GLY 11.4 g/100 g
INACTIVE INGREDIENTS: BUTYLATED HYDROXYTOLUENE; CARBOXYMETHYLCELLULOSE SODIUM, UNSPECIFIED FORM; CYCLOMETHICONE 5; PPG-14 BUTYL ETHER; STEARYL ALCOHOL; HIGH DENSITY POLYETHYLENE; HYDROGENATED CASTOR OIL; PEG-8 DISTEARATE; SILICON DIOXIDE; MEDIUM-CHAIN TRIGLYCERIDES; HYDRATED SILICA; MALTODEXTRIN; STARCH, CORN

Degree - Motionsense UltraClear Black and White Invisible Solid 48H Antiperspirant

Active ingredient

Aluminum Zirconium Tetrachlorohydrex GLY (11.4 %)

Purpose

antiperspirant

Uses

reduces underarm wetness

Warnings

- For external use only.
- Do not use on broken skin.
- Ask a doctor before use if you have kidney disease.
- Stop use if rash or irritation occurs.

Keep out of reach of children. If swallowed, get medical help or contact a Poison Control Center right away.

Directions

apply to underarms only

Inactive ingredients

Cyclopentasiloxane, PPG-14 Butyl Ether, Stearyl Alcohol, Polyethylene, Hydrogenated Castor Oil, PEG-8 Distearate, Fragrance (Parfum), Silica, Caprylic/Capric Triglyceride, Sodium Starch Octerylsuccinate, Hydrated Silica, Maltodextrin, Gelatin Crosspolymer, Hydrolyzed Corn Starch, BHT, Cellulose Gum.

Questions?

Call 1-866-334-7331